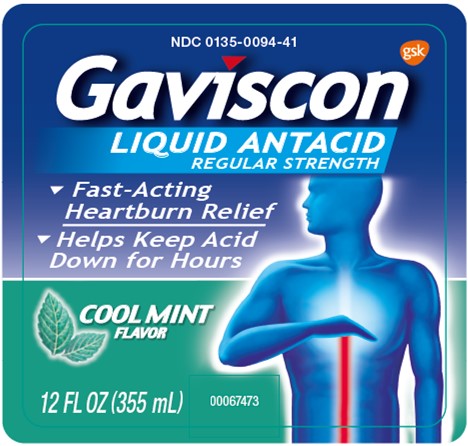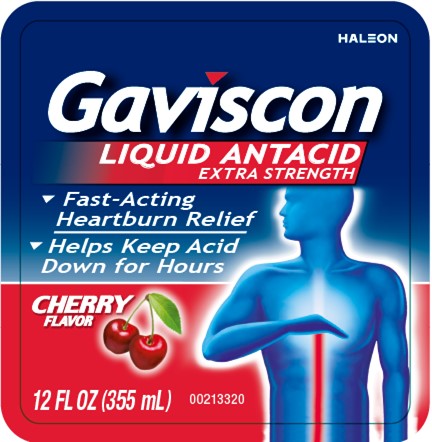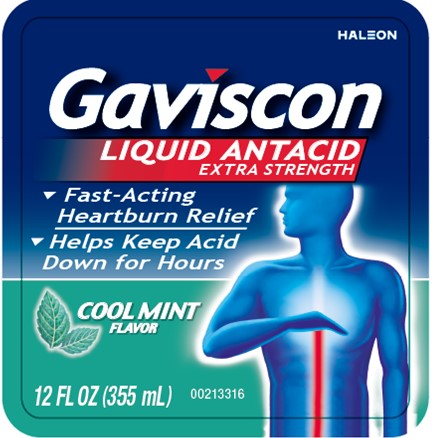 DRUG LABEL: GAVISCON
NDC: 0135-0094 | Form: LIQUID
Manufacturer: Haleon US Holdings LLC
Category: otc | Type: HUMAN OTC DRUG LABEL
Date: 20260213

ACTIVE INGREDIENTS: ALUMINUM HYDROXIDE 95 mg/15 mL; MAGNESIUM CARBONATE 358 mg/15 mL
INACTIVE INGREDIENTS: BENZYL ALCOHOL; EDETATE DISODIUM; GLYCERIN; WATER; SODIUM ALGINATE; SACCHARIN SODIUM; SORBITOL; XANTHAN GUM

Drug Facts

Active ingredients (in each 15 mL tablespoonful) Regular Strength

Aluminum hydroxide 95 mg

Magnesium carbonate 358 mg

Active ingredients (in each 5 mL / teaspoonful) Extra Strength

Aluminum hydroxide 254 mg

Magnesium carbonate 237.5 mg

Purposes

Antacid

Antacid

Uses

relieves

- heartburn
- acid indigestion
- sour stomach
- upset stomach associated with these symptoms

Warnings

Ask a doctor or pharmacist before use if you

- have kidney disease
- are on a sodium-restricted diet or a magnesium-restricted diet
- are taking a prescription drug. Antacids may interact with certain prescription drugs.

When using this product (Regular Strength)

- do not take more than 8 tablespoonfuls in 24 hours
- do not use the maximum dosage for more than 2 weeks except under the advice and supervision of a doctor
- laxative effect may occur

When using this product (Extra Strength)

- do not take more than 16 teaspoonfuls in 24 hours
- do not use the maximum dosage for more than 2 weeks, except under the advice and supervision of a doctor
- laxative effect may occur

Keep out of reach of children.

In case of overdose, get medical help or contact a Poison Control Center right away.

Directions (Regular Strength)

- shake well
- take 1-2 tablespoonfuls four times a day or as directed by a doctor
- take after meals and at bedtime
- dispense product only by spoon or other measuring device

Directions (Extra Strength)

- shake well
- take 2-4 teaspoonfuls four times a day or as directed by a doctor
- take after meals and at bedtime
- dispense product only by spoon or other measuring device

Other information (Regular Strength)

- each tablespoon (15 mL) contains:magnesium 115 mg, sodium 52 mg
- store at up to 25°C (77°F). Avoid freezing.
- keep tightly closed

Other information (Extra Strength)

- each teaspoon (5 mL) contains:magnesium 75 mg, sodium 11 mg
- store at up to 25°C (77°F). Avoid freezing.
- keep tightly closed

Inactive ingredients (Regular Strength)

benzyl alcohol, D&C yellow #10, edetate disodium, FD&C blue #1, flavor, glycerin, saccharin sodium, sodium alginate, sorbitol solution, water, xanthan gum

Inactive ingredients (Extra Strength Cool Mint)

benzyl alcohol, edetate disodium, glycerin, natural and artificial flavors, purified water, simethicone emulsion, sodium alginate, sodium saccharin, sorbitol solution, xanthan gum

Inactive ingredients (Extra Strength Cherry)

benzyl alcohol, edetate disodium, glycerin, natural and artificial flavors, purified water, simethicone emulsion, sodium alginate, sodium saccharin, sorbitol solution, xanthan gum

Questions or comments?

1-800-452-0051

Additional Information

Do not use if printed inner safety seal under cap is broken or missing.

Trademarks are owned by or licensed to the Haleon group of companies.

©2025 Haleon group of companies or its licensor.

Pat. Info www.productpats.com

Distributed by:

Haleon

Warren, NJ 07059

Made in Mexico

Principal Display Panel

NDC 0135-0094-41

Gaviscon

LIQUID ANTACID

REGULAR STRENGTH

- Fast-Acting Heartburn Relief
- Helps Keep Acid Down for Hours

COOL MINT

FLAVOR

12 FL OZ (355 mL)

FRONT: 00067473

BACK: 00067474

Principal Display Panel

HALEON

Gaviscon

LIQUID ANTACID

EXTRA STRENGTH

- Fast-Acting Heartburn Relief
- Helps Keep Acid Down for Hours

COOL MINT
FLAVOR

12 FL OZ (355 mL)

FRONT: 00213316

BACK: 00213317

Principal Display Panel

HALEON

Gaviscon

LIQUID ANTACID

EXTRA STRENGTH

- Fast-Acting Heartburn Relief
- Helps Keep Acid Down for Hours

CHERRY
FLAVOR

12 FL OZ (355 mL)

FRONT: 00213320

BACK: 00213322